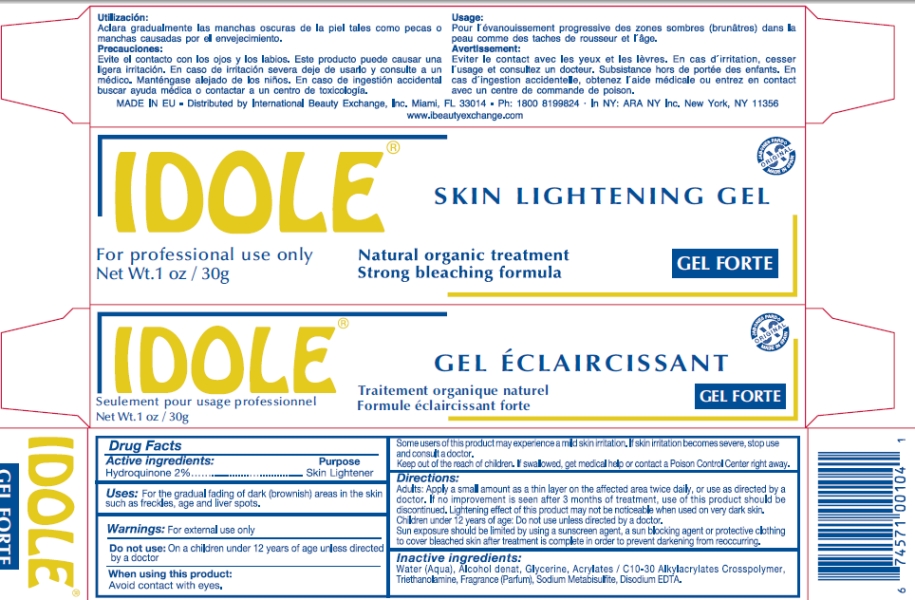 DRUG LABEL: Idole Skin Lightening
NDC: 66129-414 | Form: GEL
Manufacturer: International Beauty Exchange
Category: otc | Type: HUMAN OTC DRUG LABEL
Date: 20110311

ACTIVE INGREDIENTS: HYDROQUINONE .6 g/30 g
INACTIVE INGREDIENTS: WATER; ALCOHOL; GLYCERIN; CARBOMER COPOLYMER TYPE A; TROLAMINE; SODIUM METABISULFITE; EDETATE DISODIUM

Drug Facts

ACTIVE INGREDIENT

Hydroquinone 2%

WARNINGS

For external use only

DO NOT USE

On children less than 12 years of age unless directed by a doctor

WHEN USING

Avoid contact with the eyes

KEEP OUT OF REACH OF CHILDREN

If swallowed, get medical help or contact a Poison Control Center right away

PURPOSE

Skin lightener